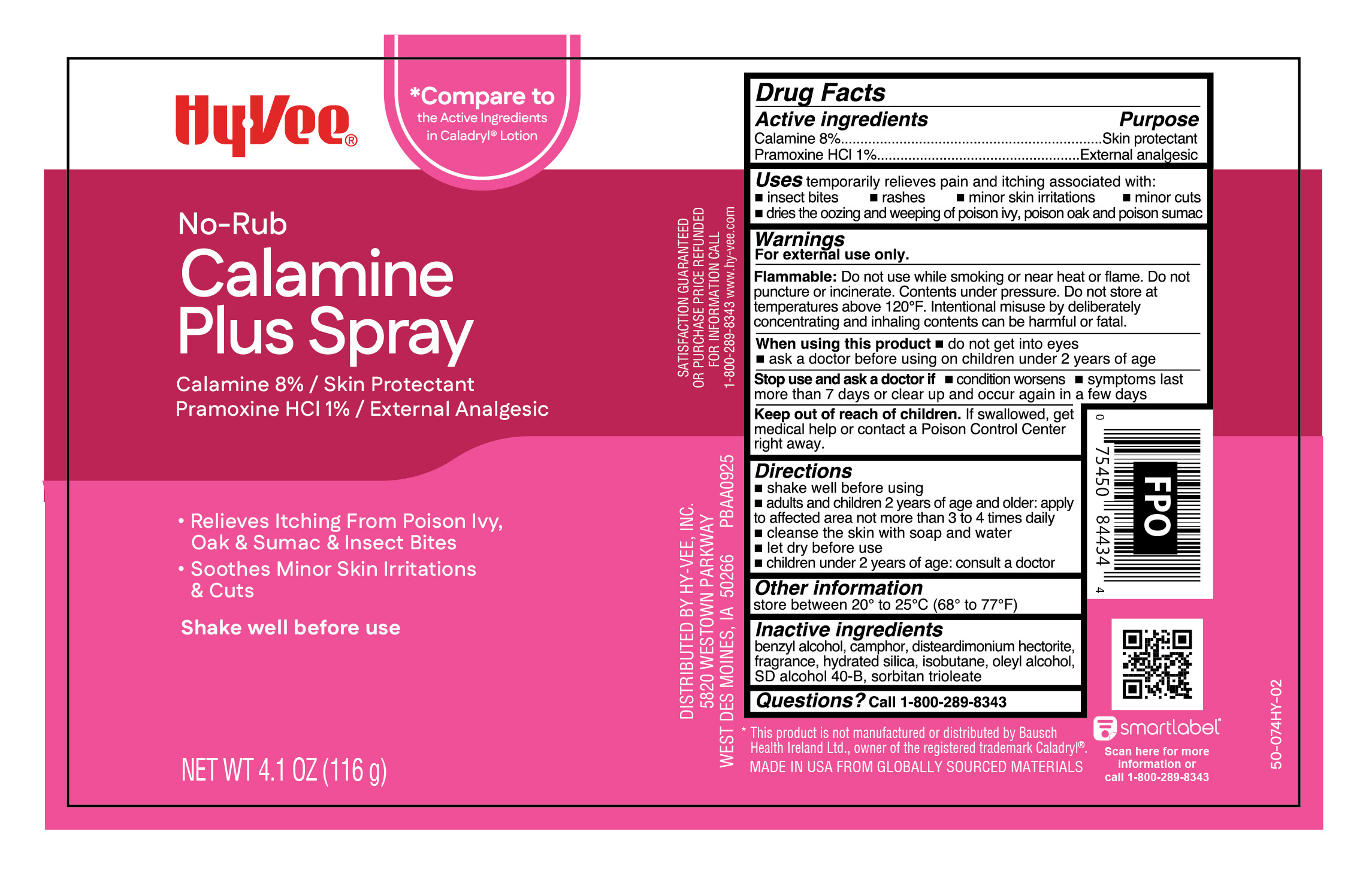 DRUG LABEL: Calamine Plus Pramoxine HCl
NDC: 42507-956 | Form: AEROSOL, SPRAY
Manufacturer: HY-VEE, INC
Category: otc | Type: HUMAN OTC DRUG LABEL
Date: 20251117

ACTIVE INGREDIENTS: FERRIC OXIDE RED 5 mg/1 g; ZINC OXIDE 75 mg/1 g; PRAMOXINE HYDROCHLORIDE 10 mg/1 g
INACTIVE INGREDIENTS: BENZYL ALCOHOL; CAMPHOR (SYNTHETIC); HYDRATED SILICA; ISOBUTANE; OLEYL ALCOHOL; SORBITAN TRIOLEATE; DISTEARDIMONIUM HECTORITE; ALCOHOL

Hy-Vee Calamine Plus Spray

Active ingredient

Calamine 8%
Pramoxine HCl 1%

Purpose

Skin protectant
External analgesic

Uses

temporarily relieves pain and itching associated with:

- insect bites
- rashes
- minor skin irritations
- minor cuts
- dries the oozing and weeping of poison ivy, poison oak and poison sumac

Warnings

For external use only.

Flammable:

Do not use while smoking or near heat or flame. Do not puncture or incinerate. Contents under pressure. Do not store at temperatures above 120°F. Intentional misuse by deliberately concentrating and inhaling contents can be harmful or fatal.

When using this product

- do not get into eyes
- ask a doctor before using on children under 2 years of age

Stop use and ask a doctor if

- conditions worsens
- symptoms last more than 7 days or clear up and occur again in a few days

Keep out of reach of children.

If swallowed, get medical help or contact a Poison Control Center right away.

Directions

- shake well before using
- adults and children 2 years of age and older: apply as needed to the affected area, not more than 3 or 4 times daily
- cleanse the skin with soap and water
- let dry before use
- children under 2 years of age: consult a doctor

Other information

store between 20° to 25°C (68° to 77°F)

Inactive ingredients

benzyl alcohol, camphor, disteardimonium hectorite, fragrance, hydrated silica, isobutane, oleyl alcohol, SD alcohol 40-B, sorbitan trioleate

Questions?

Call 1-800-289-8343

Principal Display Panel

HyVee

No-Rub

Calamine

Plus Spray

Calamine 8% / Skin Protectant

Pramoxine HCL 1% / External Analgesic

- Relieves Itching From Poison Ivy,

Oak & Sumac & Insect Bites

- Soothes Minor Skin Irritations

& Cuts

Shake well before use

NET WT 4.1 OZ (116 g)